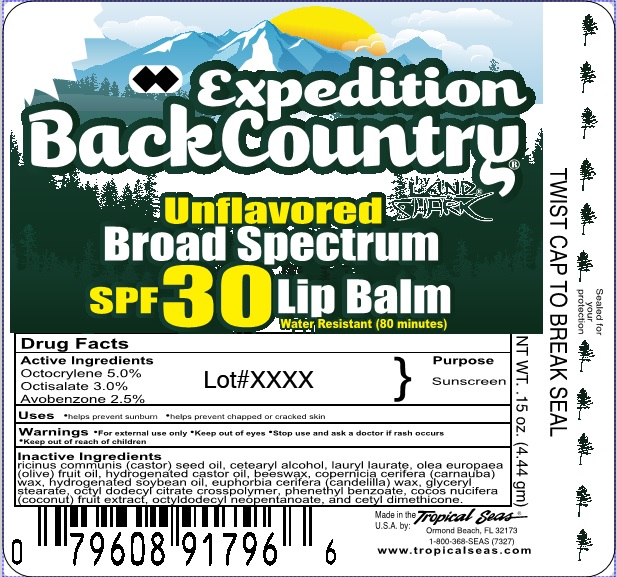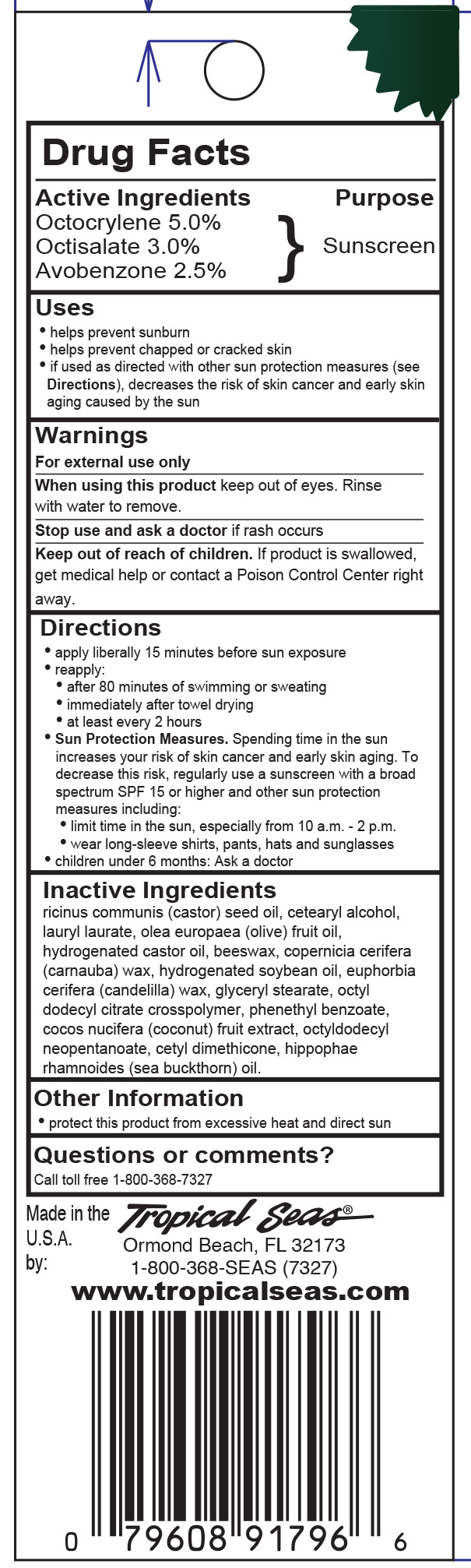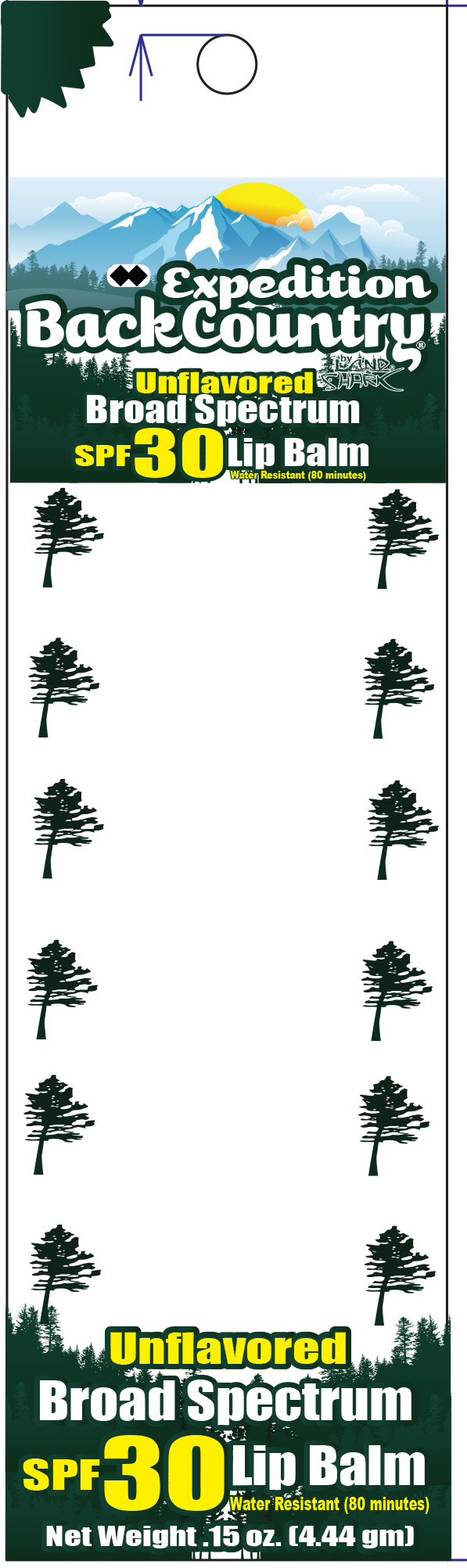 DRUG LABEL: Expedition BackCountry SPF 30
NDC: 52854-976 | Form: LIPSTICK
Manufacturer: Tropical Seas, Inc.
Category: otc | Type: HUMAN OTC DRUG LABEL
Date: 20251104

ACTIVE INGREDIENTS: OCTOCRYLENE 5 g/100 g; OCTISALATE 3 g/100 g; AVOBENZONE 2.5 g/100 g
INACTIVE INGREDIENTS: CASTOR OIL; CETOSTEARYL ALCOHOL; LAURYL LAURATE; OLIVE OIL; HYDROGENATED CASTOR OIL; YELLOW WAX; CARNAUBA WAX; HYDROGENATED SOYBEAN OIL; CANDELILLA WAX; GLYCERYL STEARATE SE; PHENETHYL BENZOATE; COCONUT; OCTYLDODECYL NEOPENTANOATE; CETYL DIMETHICONE 150; HIPPOPHAE RHAMNOIDES SEED OIL

Lip Balm Unflavored SPF 30

Drug Facts

Active Ingredients

Octocrylene 5.0%

Octisalate 3.0%

Avobenzone 2.5%

Purpose

Sunscreen

Uses

- helps prevent sunburn
- helps prevent chapped or cracked skin

Warnings

For external use only *Keep out of eyes

Stop use and ask a doctor if rash occurs

Keep out of reach of children.

Directions

- apply liberally 15 minutes before sun exposure
- reapply:
- after 80 minutes of swimming or sweating
- immediately after towel drying
- at least every 2 hours
- Sun Protection Measures. Spending time in the sun increases your risk of skin cancer and early skin aging. To decrease this risk, regularly use a sunscreen with a broad spectrum SPF 15 or higher and other sun protection measures including:
- limit time in the sun, especially from 10 a.m. - 2 p.m.
- wear long-sleeve shirts, pants, hats and sunglasses
- children under 6 months: Ask a doctor

Inactive Ingredients

ricinus communis (castor) seed oil, cetearyl alcohol, lauryl laurate, olea europaea (olive) fruit oil, hydrogenated castor oil, beeswax, copernicia cerifera (carnauba) wax, flavor, hydrogenated soybean oil, euphorbia cerifera (candelilla) wax, flavor, glyceryl stearate, octyl dodecyl citrate crosspolymer, phenethyl benzoate, cocos nucifera (coconut) fruit extract, octyldodecyl neopentanoate, cetyl dimethicone, hippophae rhamnoides (sea buckthorn) oil.

Principal Display Panel - Label

4.44g NDC 52854-927-01

4.44g NDC 52854-927-01 Blister Card Front

4.44g NDC 52854-927-01 Blister Card Back